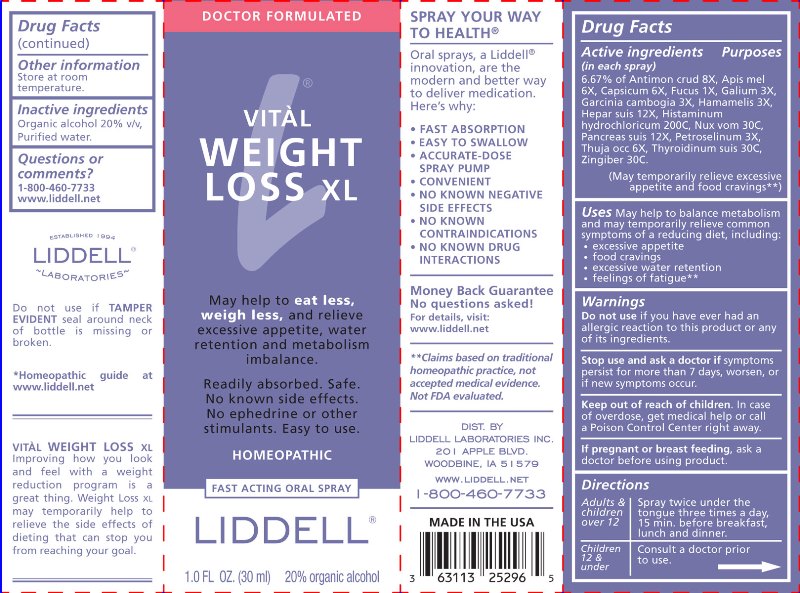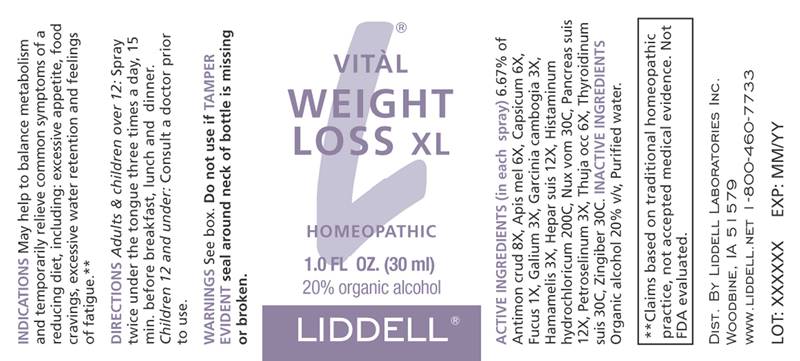 DRUG LABEL: Vital Weight Loss XL
NDC: 50845-0232 | Form: LIQUID
Manufacturer: Liddell Laboratories, Inc.
Category: homeopathic | Type: HUMAN OTC DRUG LABEL
Date: 20240701

ACTIVE INGREDIENTS: ANTIMONY TRISULFIDE 8 [hp_X]/1 mL; APIS MELLIFERA 6 [hp_X]/1 mL; CAPSICUM 6 [hp_X]/1 mL; FUCUS VESICULOSUS 1 [hp_X]/1 mL; GALIUM APARINE WHOLE 3 [hp_X]/1 mL; GARCINIA GUMMI-GUTTA FRUIT 3 [hp_X]/1 mL; HAMAMELIS VIRGINIANA ROOT BARK/STEM BARK 3 [hp_X]/1 mL; PORK LIVER 12 [hp_X]/1 mL; HISTAMINE DIHYDROCHLORIDE 200 [hp_C]/1 mL; STRYCHNOS NUX-VOMICA SEED 30 [hp_C]/1 mL; SUS SCROFA PANCREAS 12 [hp_X]/1 mL; PETROSELINUM CRISPUM WHOLE 3 [hp_X]/1 mL; THUJA OCCIDENTALIS LEAFY TWIG 6 [hp_X]/1 mL; THYROID 30 [hp_C]/1 mL; GINGER 30 [hp_C]/1 mL
INACTIVE INGREDIENTS: WATER; ALCOHOL

DRUG FACTS:

ACTIVE INGREDIENTS:

(in each spray) 6.67% of Antimonium Crudum 8X, Apis Mellifica 6X, Capsicum Annuum 6X, Fucus Vesiculosus 1X, Galium Aparine 3X, Garcinia Cambogia 3X, Hamamelis Virginiana 3X, Hepar Suis 12X, Histaminum Hydrochloricum 200C, Nux Vomica 30C, Pancreas Suis 12X, Petroselinum Sativum 3X, Thuja Occidentalis 6X, Thyroidinum Suis 30C, Zingiber Officinale 30C.

USES:

May help to balance metabolism and may temporarily relieve common symptoms of a reducing diet, including:

•excessive appetite

•food cravings

•excessive water retention

•feelings of fatigue**

**Claims based on traditional homeopathic practice, not accepted medical evidence. Not FDA evaluated.

WARNINGS:

Do not use if you have ever had an allergic reaction to this product or any of its ingredients.

Stop use and ask a doctor if symptoms persist, worsen or if new symptoms occur.

Keep out of reach of children. In case of overdose, get medical help or call a Poison Control Center right away.

If pregnant or breast feeding, ask a doctor before using product.

Other information Store at room temperature.

Do not use if TAMPER EVIDENT seal around neck of bottle is missing or broken.

Keep out of reach of children. In case of overdose, get medical help or call a Poison Control Center right away.

DIRECTIONS:

Adults & children over 12: Spray twice under the tongue three times a day, 15 min. before breakfast, lunch and dinner.

Children 12 & under: Consult a doctor prior to use.

INDICATIONS:

May help to balance metabolism and may temporarily relieve common symptoms of a reducing diet, including:
•excessive appetite
•food cravings
•excessive water retention
•feelings of fatigue**

**Claims based on traditional homeopathic practice, not accepted medical evidence. Not FDA evaluated.

INACTIVE INGREDIENTS:

Organic alcohol 20% v/v, Purified water

QUESTIONS:

DIST. BY
LIDDELL LABORATORIES INC.
201 APPLE BLVD.
WOODBINE, IA 51579
WWW.LIDDELL.NET
1-800-460-7733

PACKAGE LABEL DISPLAY:

DOCTOR FORMULATED

VITAL
WEIGHT
LOSS XL

May help to eat less,

weigh less, and relieve

excessive appetite, water

retention and metabolism

imbalance.

Readily absorbed. Safe.

No known side effects.

No ephedrine or other

stimulants. Easy to use.

HOMEOPATHIC

FAST ACTING ORAL SPRAY

LIDDELL

1.0 FL OZ (30 ml)